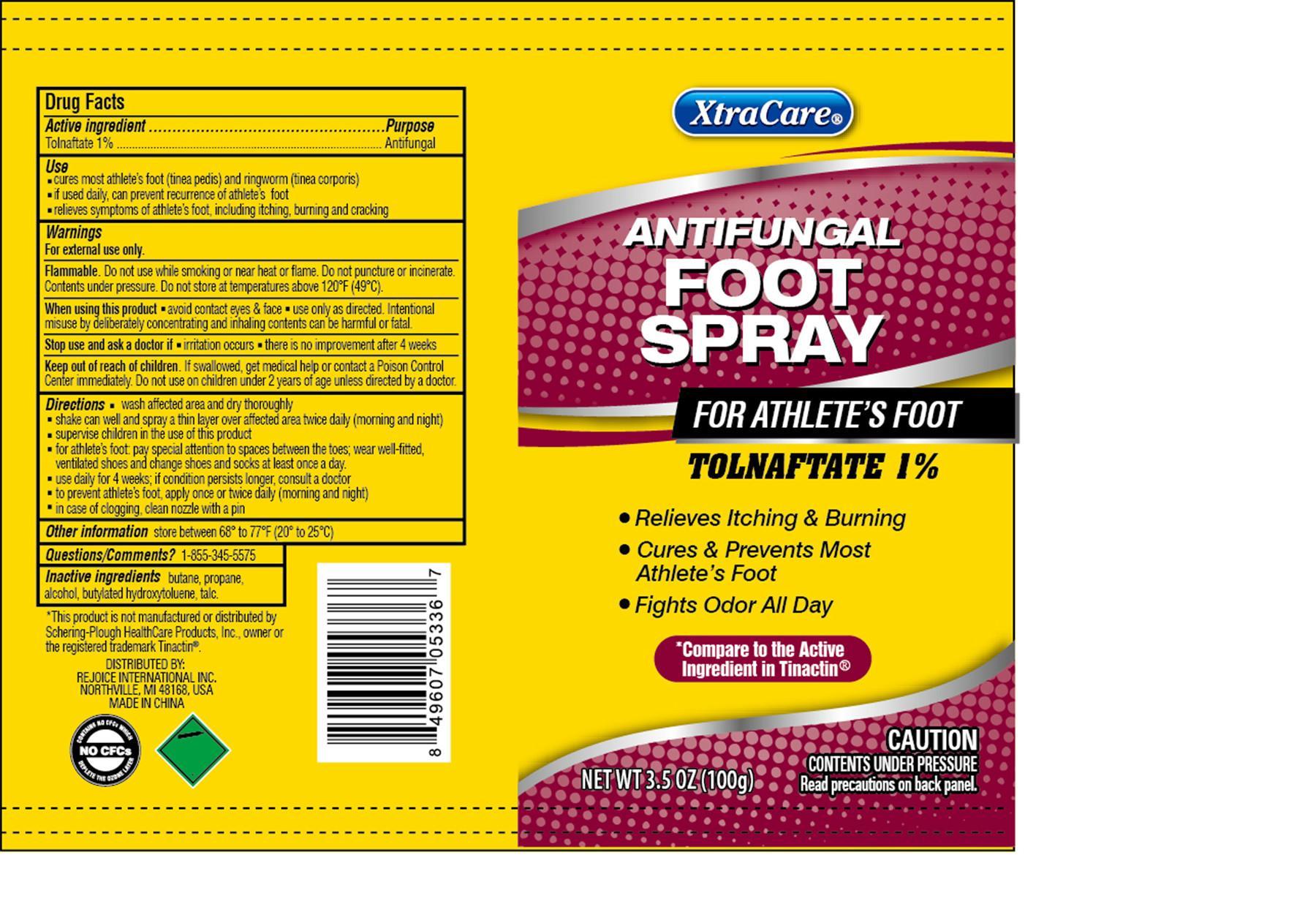 DRUG LABEL: XtraCare Antifungal Foot
NDC: 57337-056 | Form: SPRAY
Manufacturer: Rejoice International
Category: otc | Type: HUMAN OTC DRUG LABEL
Date: 20190913

ACTIVE INGREDIENTS: TOLNAFTATE 1 g/100 g
INACTIVE INGREDIENTS: BUTANE; PROPANE; ALCOHOL; BUTYLATED HYDROXYTOLUENE; TALC

XtraCare Antifungal Foot

Active Ingredient ............................................ Purpose

Tolnaftate 1% .................................................. Antifungal

Use

- cures most athlete's foot (tinea pedis) and ringworm (tinea corporis)
- if used daily, can prevent recurrence of athlete's foot
- relieves symptoms of athlete's foot, including itching, burning and cracking

Keep out of reach of children. If swallowed, get medical help or contact a Poison Control Center immediately. Do not use on children under 2 years of age unless directed by a doctor.

INDICATIONS AND USAGE

XtraCare® Antifungal Foot Spray

For Athlete's Foot

Tolnaftate 1%

- Relieves Itching & Burning
- Cures & Prevents Most Athlete's Foot
- Fights Odor All Day

*Compare to the Active Ingredient in Tinactin®

CAUTION Contents under pressure - Read precautions on back panel.

Net Wt 3.5 Oz (100g)

Warnings

For external use only.

Flammable. Do not use while smoking or near heat or flame. Do not puncture or incinerate. Contents under pressure. Do not store at temperatures above 120oF (49oC).

When using this product

- avoid eyes & face
- use only as directed. Intentional misuse by deliberately concentrating and inhaling contents can be harmful or fatal.

Stop use and ask a doctor if

- irritation occurs
- there is no improvement after 4 weeks

Directions

- wash affected area and dry thoroughly
- shake can well and spray a thin layer over affected area twice daily (morning and night)
- supervise children in the use of this product
- for athlete's foot: pay special attention to spaces betwen the toes; wear well-fitted, ventilated shoes and change shoes and socks at least once a day.
- use daily for 4 weeks; if condition persists longer, consult a doctor
- to prevent athlete's foot, apply once or twice daily (morning and night)
- in case of clogging, clean nozzle with a pin

Inactive Ingredients

butane, propane, alcohol, butylated hydroxytoluene, talc.

Other information store between 68o to 77oF (20o to 25oC)

Questions/Comments? 1-855-345-5575

*This product is not manufactured or distributed by Schering-Plough HealthCare Products, Inc., owner of the registered trademark Tinactin®

DISTRIBUTED BY

REJOICE INTERNATIONAL, INC

NORTHVILLE, MI 48168 USA

MADE IN CHINA